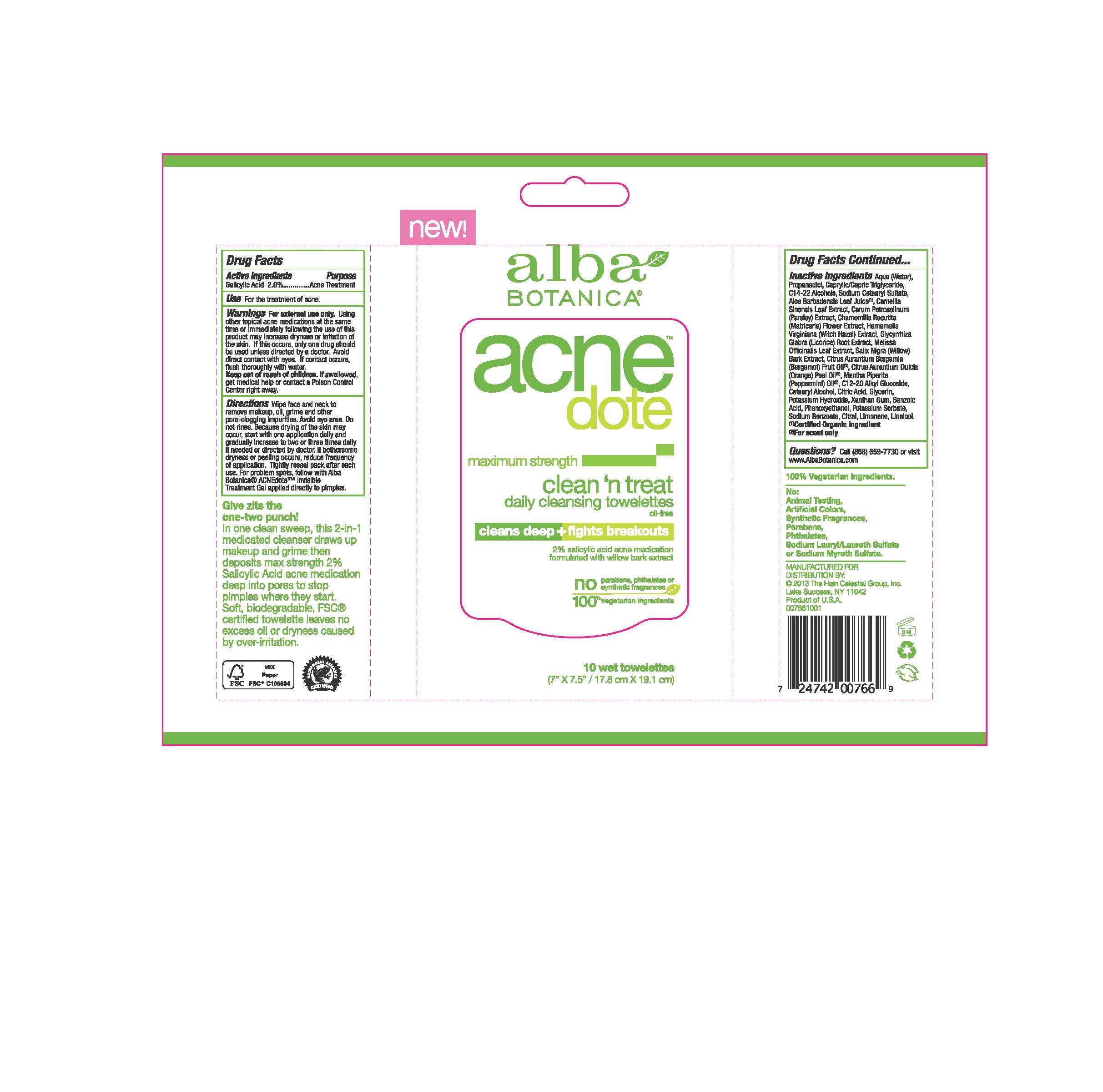 DRUG LABEL: Alba Acnedote Clean Treat Cleansing Towelette
NDC: 61995-2766 | Form: CLOTH
Manufacturer: The Hain Celestial Group, Inc.
Category: otc | Type: HUMAN OTC DRUG LABEL
Date: 20141121

ACTIVE INGREDIENTS: SALICYLIC ACID 2 g/10 1
INACTIVE INGREDIENTS: SODIUM CETOSTEARYL SULFATE; POTASSIUM SORBATE; GLYCYRRHIZA GLABRA; BERGAMOT OIL; SALIX ALBA BARK; WATER; GLYCERIN; ALOE VERA LEAF; ORANGE OIL; PROPANEDIOL; MEDIUM-CHAIN TRIGLYCERIDES; C14-22 ALCOHOLS; PEPPERMINT OIL; HAMAMELIS VIRGINIANA TOP WATER; PARSLEY; CHAMOMILE; MELISSA OFFICINALIS LEAF; C12-20 ALKYL GLUCOSIDE; CETOSTEARYL ALCOHOL; ANHYDROUS CITRIC ACID; POTASSIUM HYDROXIDE; XANTHAN GUM; BENZOIC ACID; PHENOXYETHANOL; SODIUM BENZOATE

Active Ingredient

Salicylic Acid 2.0%

DOSAGE AND ADMINISTRATION

Wipe face and neck to remove makeup, oil, grime and other pore clogging impurities. Avoid eye area. Do not rinse. Because drying of the skin may occur, start with one application daily and gadually increase to two or three times daily if needed or directed by doctor. If bothersome dryness or peeling occurs, reduce frequency of application.

PURPOSE

Acne Treatment

WARNINGS

For external use only. Using other topical acne medications at the same time or immediately following the use of this product may increase dryness and irritation of the skin. If this occurs, only one drug should be used unless directed by a doctor. Avoid direct contact with eyes. If contact occurs, flush throughly with water.

Keep out of reach of children. If swallowed get medical help or contact Poison Center right away.

INACTIVE INGREDIENT

Water, Propanediol, Caprylic/Capric Triglyceride, C14-22 Alcohols, Sodium Cetearyl Sulfate, Aloe Barbadensis Leaf Juice(1), Hamamelis Verginiana (Witch Hazel) Water, Camellia Sinensis Leaf Extract (1), Chamomilla Recutita (Matricaria) Flower Extract (1), Carum Petroselinum (Parsley) Extract, Glycyrrhiza Glabra (Licorice) Roo Exxtract, Salix Alba (Willow) Bark Extract (1),Citrus Aurantium Dulcis (Orange) Peel Oil (2), Citrus Aurantium Bergamia (Bergamot) Oil (2), Mentha Piperita (Peppermint) Oil (2), C12-20 Alkyl Glucoside, Cetearyl Alcohol, Citric Acid, Glycerin, Potassium Hydroxude, Xanthan Gum, Benzoic Acid, Phenoxyethanol, Potassium Sorbate, Sodium Benzoate.

(1) Certified Organicf Ingredient; (2) For scent only

INDICATIONS AND USAGE

For the treatment of acne.